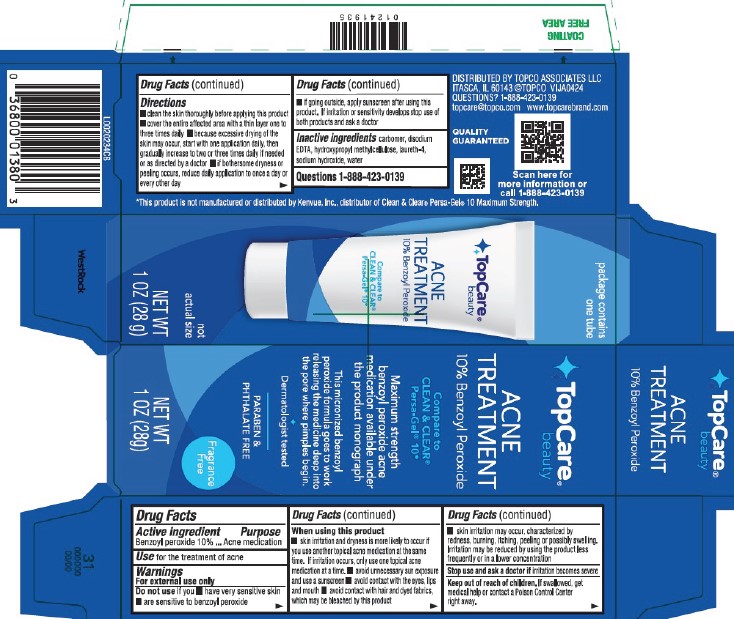 DRUG LABEL: Acne Treatment
NDC: 76162-229 | Form: GEL
Manufacturer: Topco Associates LLC
Category: otc | Type: HUMAN OTC DRUG LABEL
Date: 20260213

ACTIVE INGREDIENTS: BENZOYL PEROXIDE 100 mg/1 g
INACTIVE INGREDIENTS: CARBOMER HOMOPOLYMER, UNSPECIFIED TYPE; EDETATE DISODIUM; HYPROMELLOSE, UNSPECIFIED; LAURETH-4; SODIUM HYDROXIDE; WATER

Top Care 229.001/229AC-AD
10% Benzoyl Peroxide Acne Medicated Gel

Active ingredient

Benzoyl peroxide 10%

Purpose

Acne medication

Use

for the treatment of acne

Warnings

For external use only

Do not use if you

- have very sensitive skin
- are sensitive to benzoyl peroxide

When using this product

- skin irritation and dryness is more likely to occur if you use aother topical acne medication at the same time. If irritation occurs, only use one topical acne medication at a time
- avoid unnecessary sun exposure and use a sunscreen
- avoid contact with eyes, lips and mouth
- avoid contact with hair and dyed fabrics, which may be bleached by this product
- skin irritation may occur, characterized by redness, burning, itching, peeling or possible swelling. Irritation may be reduced by using the product less frequently or in a lower concentration

stop use and ask a doctor if

irritation becomes severe

Keep out of reach of children.

If swallowed, get medical help or contact a Poison Control Center right away.

Directions

- clean the skin thoroughly before applying this product
- cover the entire affected area with a thin layer one to three times daily
- because excessive drying of the skin may occur, start with one application daily, then gradually increase to two or three times daily if needed or as directed by a doctor
- if bothersome dryness or peeling occurs, reduce daily application to once a day or every other day
- if going outside, apply sunscreen after using this product. If irritation or sensitivity develops stop use of both products and ask a doctor

inactive ingredients

carbomer, disodium EDTA, hydroxypropyl methylcellulose, laureth-4, sodium hydroxide, water

Questions

1-888-423-0139

Disclaimer

*This product is not manufactured or distributed by Kenvue, Inc., distributor of Clean & Clear®Persa-Gel®10 Maximum Strength.

Adverse Reaction

DISTRIBUTED BY TOPCO ASSOCIATES LLC

Itasca, IL 60143 ©TOPCO VIJA0424

QUESTIONS? 1-888-423-0139

topcare@topco.com

www.topcarebrand.com

Quality Guaranteed

Scan here for more information or call 1-888-423-0139

principal display panel

TopCare®Beauty

ACNE TREATMENT

10% Benzoyl Peroxide

Compare to CLEAN & CLEAR®Persa-Gel®10*

Maximum strength benzoyl peroxide acne medication available under the product monograph

This micronized benzoyl peroxide formula goes to work releasing the medicine deep into the pore where pimples begin.

Dermatologist Tested

PARABEN & PHTHALATE FREE

Fragrance Free

NET WT 1 OZ (28 g)

package contains one tube

not actual size

NET WT 1 OZ (28 g)